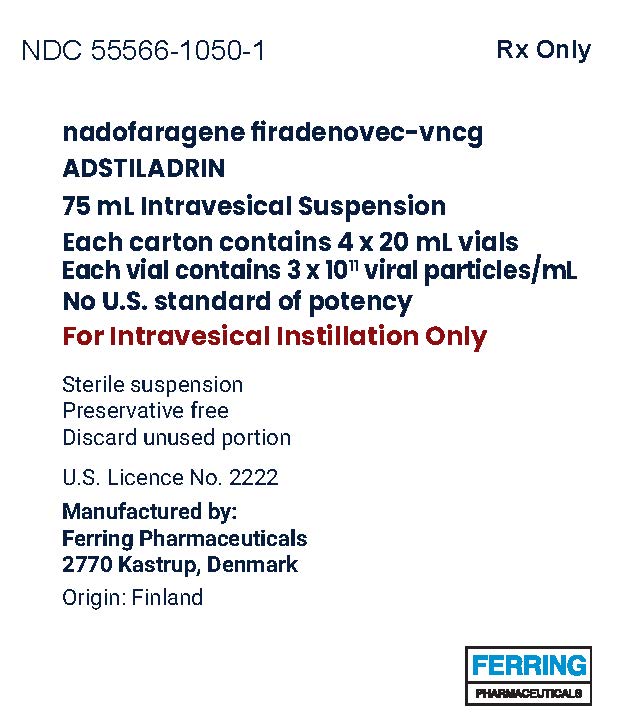 DRUG LABEL: ADSTILADRIN
NDC: 55566-1050 | Form: SUSPENSION
Manufacturer: Ferring Pharmaceuticals Inc.
Category: prescription | Type: HUMAN PRESCRIPTION DRUG LABEL
Date: 20251010

ACTIVE INGREDIENTS: NADOFARAGENE FIRADENOVEC 300000000000 {VP}/1 mL
INACTIVE INGREDIENTS: (N-(3-CHOLAMIDOPROPYL)-N-(3-LACTOBIONAMIDOPROPYL))CHOLAMIDE 0.95 mg/1 mL; CITRIC ACID MONOHYDRATE 0.01 mg/1 mL; TRISODIUM CITRATE DIHYDRATE 0.04 mg/1 mL; POLYSORBATE 80 0.48 mg/1 mL; HYDROXYPROPYL BETADEX 7.9 mg/1 mL; SODIUM PHOSPHATE, MONOBASIC, DIHYDRATE 1.4 mg/1 mL; TROMETHAMINE 1.4 mg/1 mL; SUCROSE 17 mg/1 mL; MAGNESIUM CHLORIDE 0.34 mg/1 mL; GLYCERIN 84 mg/1 mL; WATER

HIGHLIGHTS OF PRESCRIBING INFORMATION

These highlights do not include all the information needed to use ADSTILADRIN® safely and effectively. See full prescribing information for ADSTILADRIN.
ADSTILADRIN® (nadofaragene firadenovec-vncg) suspension, for intravesical use
Initial U.S. Approval: 2022

1 INDICATIONS AND USAGE

ADSTILADRIN is a non-replicating adenoviral vector-based gene therapy indicated for the treatment of adult patients with high-risk Bacillus Calmette-Guérin (BCG)-unresponsive non-muscle invasive bladder cancer (NMIBC) with carcinoma in situ (CIS) with or without papillary tumors. (1)

2 DOSAGE AND ADMINISTRATION

- Premedication with an anticholinergic is recommended before each instillation of ADSTILADRIN. (2.1)
- Administer ADSTILADRIN by intravesical instillation only. (2.1)
- ADSTILADRIN is not for intravenous use, topical use, or oral administration.
- The dose is 75 mL of ADSTILADRIN at a concentration of 3 x 10^11 viral particles (vp)/mL, instilled once every three (3) months. (2.1)
- Allow ADSTILADRIN to be left in the bladder for 1 hour following instillation

3 DOSAGE FORMS AND STRENGTHS

ADSTILADRIN is a suspension for intravesical instillation, supplied as single-use vials. (3)
ADSTILADRIN is provided in a carton containing four (4) vials. All vials have a nominal concentration of 3 × 10^11 viral particles (vp)/mL. Each vial of ADSTILADRIN contains an extractable volume of not less than 20 mL. (3)

4 CONTRAINDICATIONS

ADSTILADRIN is contraindicated in patients with hypersensitivity to interferon alfa or any component of the product. (4)

5 WARNINGS AND PRECAUTIONS

- Delaying cystectomy could lead to the development of metastatic bladder cancer, which can be lethal. (5.1)
- Risk of disseminated adenovirus infection: Persons who are immunocompromised or immunodeficient may be at risk for disseminated infection from ADSTILADRIN due to low levels of replication-competent adenovirus. Avoid ADSTILADRIN exposure to immunocompromised or immunodeficient individuals. (5.2)

6 ADVERSE REACTIONS

The most common (>10%) adverse reactions, including laboratory abnormalities (>15%), were glucose increased, instillation site discharge, triglycerides increased, fatigue, bladder spasm, micturition (urination urgency), creatinine increased, hematuria (blood in urine), phosphate decreased, chills, pyrexia (fever), and dysuria (painful urination). (6.1)

To report SUSPECTED ADVERSE REACTIONS, contact Ferring Pharmaceuticals at 1-888-337-7464 or FDA at 1-800-FDA-1088 or www.fda.gov/medwatch.

8 USE IN SPECIFIC POPULATIONS

Immunocompromise/immunodeficiency: Avoid in patients with immunocompromise or immunodeficiency. (8)

FULL PRESCRIBING INFORMATION

1 INDICATIONS AND USAGE

ADSTILADRIN® is indicated for the treatment of adult patients with high-risk Bacillus Calmette-Guérin (BCG)-unresponsive non-Muscle Invasive Bladder Cancer (NMIBC) with carcinoma in situ (CIS) with or without papillary tumors.

2 DOSAGE AND ADMINISTRATION

Important Administration Instructions

ADSTILADRIN is for intravesical instillation only.

ADSTILADRIN is not for intravenous use, topical use, or oral administration.

2.1 Dose

The recommended dose of ADSTILADRIN is 75 mL at a concentration of 3 x 10^11 viral particles (vp)/mL instilled once every three (3) months into the bladder via a urinary catheter [see Dosage and Administration (2.2)].

Premedication with an anticholinergic is recommended before each instillation of ADSTILADRIN.

2.2 Preparation and Handling

ADSTILADRIN is a non-replicating adenoviral vector-based gene therapy. Follow universal biosafety precautions for handling.

Individuals who are immunosuppressed or immune-deficient, should not prepare, administer, or come into contact with ADSTILADRIN [see Warnings and Precautions (5)].

ADSTILADRIN is provided as a sterile frozen suspension.

All four vials of ADSTILADRIN must be thawed and brought to room temperature (20°C to 25°C [68°F to 77°F]) prior to use.

WHEN THAWING AT ROOM TEMPERATURE

Frozen ADSTILADRIN vials will thaw in approximately 3 to 5 hours outside the cardboard nest when placed at room temperature (up to 25°C [77ºF]) (8 to 10 hours inside the nest).

WHEN THAWING IN REFRIGERATOR

Frozen ADSTILADRIN vials will thaw in approximately 4 to 5 hours outside the cardboard nest when placed in the refrigerator (up to 8°C [46ºF]) (11 to 13 hours inside the nest). Subsequent time for bringing thawed ADSTILADRIN to room temperature is approximately 2 hours 30 minutes outside of the cardboard nest (6 hours inside the nest).

Do not expose the vials to higher temperatures. Protect from light. DO NOT refreeze.

The vials may be moved between refrigerator and room temperature if the total storage time at each condition is not exceeded (24 hours at room temperature and 7 days refrigerated including thawing time).

Inspection and Preparing ADSTILADRIN for instillation

Visually inspect all 4 vials for visible particles and discoloration. The suspension is clear to slightly opalescent and may contain opalescent flecks. Do not use if visible particles or discoloration are observed. Mix gently. Do not shake.

Items required for instillation:

• Four (4) thawed vials of ADSTILADRIN

• Four (4) vented vial adapters suitable for a standard 20 mLvial

• Two (2) standard 50 or 60 mL polypropylene Luer lock syringes or one (1) Luer lock syringe equal to or greater than 75 mL (max 100 mL)

• Two (2) Luer lock adapters
- One (1) straight, or intermittent, urethral catheter with a proximal funnel opening that will accommodate the Luer lock adapter.
- Use only catheters made of vinyl/PVC (uncoated or coated with hydrogel), red rubber latex or silicone to instill ADSTILADRIN. Do not use catheters coated or embedded with silver or antibiotics.

1. Using aseptic technique, remove the cap from an ADSTILADRIN vial and attach a vented vial adapter according to manufacturer's instructions.

2. Connect the syringe to the vial adapter and withdraw the contents of the vial into the syringe. Repeat steps 1-2 for the remaining three (3) vials until 75 mL has been withdrawn into one (1) or two (2) syringes.

- The volumes in the syringes do not have to be equal.

3. Discard any remaining volume according to universal precautions.

- If unable to administer the suspension shortly after withdrawal, the solution may be stored in syringes for up to 6 hours at room temperature (20°C to 25°C [68°F to 77°F]) protected from light.

Treat any ADSTILADRIN spills or unused portion with a virucidal agent (such as sodium hypochlorite with 0.5% active chlorine or 6% hydrogen peroxide solution) for 15 minutes. Disposable materials that have come into contact with ADSTILADRIN should be placed in biohazard containers for destruction. Non-disposable equipment may be decontaminated according to the facility's standard operating procedures. [see Patient Counseling Information (17)].

2.3 Bladder instillation of ADSTILADRIN

1. Premedication with an anticholinergic before each instillation of ADSTILADRIN is recommended.
2. ADSTILADRIN must be brought to room temperature before administration [see Dosage and Administration (2.2)].
3. Before administering ADSTILADRIN to the patient, insert one straight, or intermittent, urinary catheter with a proximal funnel opening that will accommodate the Luer lock adapter.
4. Use only catheters made of vinyl/PVC (uncoated or coated with hydrogel), red rubber latex or silicone to instill ADSTILADRIN. Do not use catheters coated or embedded with silver or antibiotics.
5. Use the catheter to completely empty the patient's bladder before instillation of ADSTILADRIN. Do not remove the catheter.
6. Attach the Luer lock end of the same catheter adapter to the syringe containing ADSTILADRIN and insert the tapered end of the catheter adapter into the funnel opening of the catheter.
7. Slowly instill 75 mL of ADSTILADRIN into the bladder through the catheter, ensuring that the complete volume is administered.
8. After the instillation, ADSTILADRIN should be retained in the bladder for 1 hour. During the 1-hour dwell time, the patient should reposition approximately every 15 minutes from left to right, back and abdomen to maximize bladder surface exposure. If, during the dwell time, the patient exhibits bladder cramping or premature voiding, repositioning of the patient may be adjusted or discontinued.
9. Evacuate ADSTILADRIN from the bladder as part of routine emptying of the bladder, or the patient may void and completely empty the bladder after 1 hour has elapsed.
10. Voided urine should be disinfected for 15 minutes with an equal volume of virucidal agent before flushing of the toilet. [see Patient Counseling Information (17)].

3 DOSAGE FORMS AND STRENGTHS

ADSTILADRIN is a sterile, clear to opalescent suspension for intravesical instillation, supplied as single-use vials.

ADSTILADRIN is provided in a carton containing four (4) vials. All vials have a nominal concentration of 3 × 10^11 viral particles (vp)/mL. Each vial of ADSTILADRIN contains an extractable volume of not less than 20 mL.

4 CONTRAINDICATIONS

ADSTILADRIN is contraindicated in patients with prior hypersensitivity reactions to interferon alfa or to any component of the product [see Description (11)].

5 WARNINGS AND PRECAUTIONS

5.1 Risk of Muscle Invasive or Metastatic Bladder Cancer with Delayed Cystectomy

Delaying cystectomy in patients with BCG-unresponsive CIS could lead to development of muscle invasive or metastatic bladder cancer, which can be lethal. The risk of developing muscle-invasive or metastatic bladder cancer increases the longer cystectomy is delayed in the presence of persisting CIS.

Of the patients with CIS treated with ADSTILADRIN on Study CS-003 who underwent subsequent radical cystectomy and for whom pathologic data were available, 14% (n = 6) had muscle-invasive (T2 or greater) disease at cystectomy. Median time from persistence or recurrence of CIS to cystectomy in these patients was 235 days (range 38 to 582 days). Two additional patients who did not undergo cystectomy experienced progression to muscle-invasive disease during the treatment period.

If patients with CIS do not have a complete response to treatment after 3 months or if CIS recurs, consider cystectomy.

5.2 Risk of Disseminated Adenovirus Infection

Immunocompromised persons, including those receiving immunosuppressant therapy, may be at risk for disseminated adenovirus infection because of the possible presence of low levels of replication-competent adenovirus in ADSTILADRIN. Individuals who are immunosuppressed or immune-deficient should not come into contact with ADSTILADRIN.

6 ADVERSE REACTIONS

6.1 Clinical Trials Experience

Because clinical trials are conducted under widely varying conditions, adverse reaction rates observed in the clinical trials of a drug cannot be directly compared to rates in the clinical trials of another drug and may not reflect the rates observed in practice.

The safety of ADSTILADRIN was evaluated in Study CS-003, a multicenter, single-arm, open-label study in 157 U.S. patients [see Clinical Studies (14)] with high-risk BCG‑unresponsive NMIBC, 107 of whom had BCG-unresponsive carcinoma in situ (CIS) with or without papillary tumors.

Patients received 75 mL (3 x 10^11 vp/mL) ADSTILADRIN administered intravesically once every 3 months for up to 12 months [see Clinical Studies (14)]. All patients with an absence of high-risk recurrence or progression were offered continued treatment every 3 months beyond 12 months. The median number of instillations of ADSTILADRIN was 2 (range 1 to 5).

Serious adverse reactions occurred in 11% of patients who received ADSTILADRIN. Serious adverse reactions occurring in >1% of patients included coronary artery disease and hematuria (blood in urine).

Permanent discontinuation of ADSTILADRIN due to an adverse reaction occurred in 3 (1.9%) patients. Adverse reactions that resulted in permanent discontinuation of ADSTILADRIN included bladder spasm instillation site discharge, and benign neoplasm of the bladder.

Dosage interruptions of ADSTILADRIN due to an adverse reaction occurred in 54 (34%) patients. Adverse reactions in >10% of patients that required dosage interruption included instillation site discharge, bladder spasm, and micturition urgency.

The most common (>10%) adverse reactions, including laboratory abnormalities (>15%), were glucose increased, instillation site discharge, triglycerides increased, fatigue, bladder spasm, micturition (urination) urgency, creatinine increased, hematuria (blood in urine), phosphate decreased, chills, dysuria, and pyrexia (fever).

Tables 1 and 2 summarize adverse reactions and laboratory abnormalities, respectively, in patients on ADSTILADRIN in CS-003.

Clinically relevant adverse reaction in <10% of patients who received ADSTILADRIN include syncope (fainting) (1.3%).

Table 1: Adverse Reactions (>10%) in Patients with NMIBC in CS-003
Adverse Reaction [Graded per NCI CTCAE v4.03; there were no Grade 4 or 5 reactions.] | ADSTILADRIN (n=157) (%)
Adverse Reaction [Graded per NCI CTCAE v4.03; there were no Grade 4 or 5 reactions.] | Grade 1 and 2 % | Grade 3 %
General disorders and administration site conditions | - | -
Instillation site discharge | 33 | 0
Fatigue | 24 | 0
Pyrexia | 16 | 0
Chills | 15 | 0
Renal and urinary disorders | - | -
Bladder spasm | 20 | 1
Micturition urgency | 19 | 1
Hematuria | 17 | 1
Dysuria | 16 | 0

Clinically relevant adverse reactions in <10% of patients who received ADSTILADRIN included coronary artery disease (1.3%), acute coronary syndrome (1.3%), atrial fibrillation (1.3%), dehydration (1.3%), hypoglycemia (low blood sugar) (1.3%), syncope (fainting) (1.3%), heart failure (0.6%), pericarditis, (0.6%), brain edema (swelling) (0.6%), bile duct stone (0.6%), and sepsis (0.6%).

Table 2 summarizes the laboratory abnormalities in CS-003.

Table 2: Selected Laboratory Abnormalities (>15.0%) That Worsened from Baseline in Patients with NMIBC in CS-003
Laboratory Abnormality | ADSTILADRIN [The denominator used to calculate the rate varied from 148 to 156 based on the number of patients with a baseline value and at least one post-treatment value.] (All Grades, %) | ADSTILADRIN (Grade 3 or 4, %)
Chemistry | - | -
Glucose increased | 38 | 6
Triglycerides increased | 30 | 1.9
Creatinine increased | 17 | 0
Phosphate decreased | 16 | 1.4
Hematology | - | -
Hemoglobin decreased | 16 | 0.6

8 USE IN SPECIFIC POPULATIONS

8.1 Pregnancy

Risk Summary

Adequate and well-controlled studies with ADSTILADRIN have not been conducted in pregnant women. Animal reproductive and developmental toxicity studies have not been conducted with ADSTILADRIN. Advise pregnant women of the potential risk to a fetus.

In the U.S. general population, the estimated background risk of major birth defects and miscarriage in clinically recognized pregnancies is 2 to 4% and 15 to 20%, respectively.

8.2 Lactation

Risk Summary

There is no information regarding the presence of ADSTILADRIN in human milk, the effects on the breastfed infant, or the effects on milk production. The developmental and health benefits of breastfeeding should be considered along with the mother's clinical need for ADSTILADRIN and any potential adverse effects on the breastfed infant from ADSTILADRIN or from the underlying maternal condition.

8.3 Females and Males of Reproductive Potential

No nonclinical or clinical studies were performed to evaluate the effect of ADSTILADRIN on fertility.

Pregnancy Testing

Verify pregnancy status in females of reproductive potential prior to initiating ADSTILADRIN.

Contraception

Females
Advise females of reproductive potential to use effective contraception during treatment with ADSTILADRIN and for 6 months following the last dose.

Males
Advise male patients with female partners of reproductive potential to use effective contraception during treatment with ADSTILADRIN and for 3 months following the last dose.

8.4 Pediatric Use

Safety and effectiveness of ADSTILADRIN in pediatric patients have not been established.

8.5 Geriatric Use

Clinical studies of ADSTILADRIN in BCG-unresponsive high-risk NMIBC with CIS did not include sufficient numbers of patients younger than 65 years of age to determine whether safety and effectiveness differ from older patients.

8.6 Gender-specific Use

In clinical studies with ADSTILADRIN, no overall differences in safety or efficacy were observed between females and males.

11 DESCRIPTION

ADSTILADRIN (nadofaragene firadenovec-vncg) is a non-replicating adenoviral vector-based gene therapy for intravesical instillation.

It is a recombinant adenovirus serotype 5 vector containing a transgene encoding the human interferon alfa-2b (IFNα2b).

ADSTILADRIN has a nominal concentration of 3 x 10^11 vp/mL.

A single-use vial of ADSTILADRIN contains an extractable volume of 20 mL and the following excipients: [N-(3-cholamidopropyl)-N-(3-lactobionamidopropyl)]-cholamide (Syn3) (0.95 mg/mL), citric acid monohydrate (0.01 mg/mL), glycerol (84 mg/mL), hydroxypropyl-beta-cyclodextrin (7.9 mg/mL), magnesium chloride hexahydrate (0.34 mg/mL), polysorbate 80 (Tween 80) (0.48 mg/mL), sodium dihydrogen phosphate dihydrate (1.4 mg/mL), sucrose (17 mg/mL), tri-sodium citrate dihydrate (0.04 mg/mL), tromethamine (1.4 mg/mL) and Water for Injection (q.s. 1 mL).

ADSTILADRIN is a sterile, clear to opalescent suspension, and contains no preservative.

12 CLINICAL PHARMACOLOGY

12.1 Mechanism of Action

ADSTILADRIN is a non-replicating adenoviral vector-based gene therapy designed to deliver a copy of a gene encoding a human interferon-alfa 2b (IFNα2b) to the bladder urothelium. Intravesical instillation of ADSTILADRIN results in cell transduction and transient local expression of the IFNα2b protein that is anticipated to have anti-tumor effects.

12.2 Pharmacodynamics

A Phase 1 first-in-human study was performed to determine the safety, tolerability, and maximum tolerated dose (MTD) of ADSTILADRIN in 17 patients with BCG-unresponsive NMIBC. Five dose levels (3 x 10^9 vp/mL, 1 x 10^10 vp/mL, 3 x 10^10 vp/mL, 1 x 10^11 vp/mL, and 3 x 10^11 vp/mL; all in a dose volume of 75 mL) of ADSTILADRIN were tested and quantifiable concentrations of the pharmacodynamic marker IFNα2b protein were detected in the urine of all patients, with the exception of two patients at the lowest dose level. Measurable concentrations of urine IFNα2b protein up to Day 10 post-dose suggested expression of IFNα2b in the bladder. In a Phase 2 study, all patients had quantifiable concentrations of IFNα2b protein in the urine at Day 2 after dosing with ADSTILADRIN at two different dose levels (1 x 10^11 vp/mL and 3 x 10^11 vp/mL). Measurable concentrations of urine IFNα2b protein was detected up to Day 12 post-dose. This was more common in patients at the high dose level.

Generally, higher IFNα2b concentrations and exposure were observed with increasing doses of ADSTILADRIN.

12.3 Pharmacokinetics

Nonclinical data

Human IFN protein in urine, and vector-specific DNA in blood and tissue samples, were detectable following ADSTILADRIN dosing in monkeys, with higher levels at higher doses. All monkeys had vector-specific DNA in the bladder tissue at necropsy on Days 8 and 98 (i.e., seven days after the first and second dose, respectively). Vector-specific DNA was also detected in a limited number of monkeys in the liver, kidney and gonad. At Day 148, only one animal showed vector-specific DNA in one tissue (kidney).

Clinical data

ADSTILADRIN biodistribution and shedding were investigated in two clinical studies. Only a single patient receiving a second dose in one study (Phase 2 study) at dose level of 3 x 10^11 vp/mL (2.25 x 10^13 vp) had measurable vector DNA in blood; no other patients in either study had measurable vector DNA at one hour post-dosing in blood. In urine, measurable vector DNA was detected in both studies. Generally, a higher frequency of detection of urine samples positive for vector-derived DNA, and persistence of vector-derived DNA, correlated with increasing dose level.

At the dose level of 3 x 10^11 vp/mL (2.25 x 10^13 vp), one patient (out of 4 enrolled) had detectable levels of vector DNA at Day 14 in the Phase 1 study and 16 subjects (out of 19 at visit) had detectable levels of vector DNA at Day 12 in the Phase 2 study.

13 NONCLINICAL TOXICOLOGY

13.1 Carcinogenesis, Mutagenesis, Impairment of Fertility

No animal studies have been conducted to evaluate the effects of ADSTILADRIN on carcinogenesis, mutagenesis, or impairment of fertility.

13.2 Animal Toxicology and/or Pharmacology

In cynomolgus monkeys, two repeat intravesical administrations of ADSTILADRIN of either 2.5 x 10^11 or 1.25 x 10^13 viral particles (1 x 10^10 or 5x10^11 viral particles/mL, 90 days apart) were associated with inflammation, urothelial hyperplasia, cytoplasmic vacuolation, and focal/multifocal ulceration in the urinary bladder and irritation in the ureter and urethra at necropsy 7 days after the first and second doses. Near complete resolution of these findings was observed following the 57-day recovery period after the second administration, with minimal fibrosis in the lamina propria of the bladder in a limited number of monkeys. Both dose level groups developed antibodies to the adenovirus and human interferon protein.

14 CLINICAL STUDIES

The efficacy of ADSTILADRIN was evaluated in CS-003 (NCT02773849), an open-label, multicenter, single-arm trial in 103 adults with BCG-unresponsive, high-risk, non-muscle invasive bladder cancer with carcinoma in situ (CIS) with or without papillary tumors following transurethral resection, of whom 98 were considered evaluable for response. BCG-unresponsive high-risk NMIBC was defined as persistent disease following adequate BCG therapy, disease recurrence after an initial tumor-free state following adequate BCG therapy, or T1 disease following a single induction course of BCG. Adequate BCG was defined as the administration of at least five of six doses of an initial induction course plus either of: at least two of three doses of maintenance therapy or at least two of six doses of a second induction course. Prior to treatment, all patients had undergone transurethral resection of bladder tumor (TURBT) to remove all resectable disease (Ta and T1 components). Residual CIS (Tis components) not amenable to complete resection was allowed. The trial excluded patients with extra-vesical (i.e., urethra, ureter, or renal pelvis), muscle invasive (T2-T4), or metastatic urothelial carcinoma.

Patients received ADSTILADRIN 75 mL intravesical instillation (3 x 10^11 vp/mL) once every three months for up to 12 months (four doses) or until unacceptable toxicity or recurrent high-grade (HG) NMIBC. Patients without evidence of HG recurrence were allowed to continue ADSTILADRIN treatment every three months.

The major efficacy outcome measures were complete response (CR) at any time (as defined by negative results for cystoscopy [with TURBT/biopsies as applicable] and urine cytology) and duration of response. Low-grade (Ta) papillary disease was not considered a recurrence for the purposes of evaluating CR. CR was assessed at 3, 6, 9, and 12 months by cystoscopy and cytology. Random bladder biopsy of five sites was conducted in patients remaining in CR at Month 12. Assessment of durability of CR subsequent to these evaluations was performed per local standards of care.

The evaluable CIS study population characteristics were median age of 70 (range 44-89) with 32% >75 years of age; 88% male, 92% White. Tumor pattern at study entry was CIS with T1 (5%), CIS with high-grade Ta (19%), and CIS (76%). The median number of instillations of prior BCG was 12 (range 8 to 18).

Efficacy results are summarized in Table 3.

Table 3: Efficacy Results in Study CS-003
Efficacy Outcome Measure | ADSTILADRIN (n=98)
Complete Response Rate, % | 51%
(95% CI) | (41%, 61%)
Duration of Response [Based on patients (n=50) that achieved a complete response; reflects period from the time complete response was achieved.] | -
Median in months (range) | 9.7 (3, 52+)
% with duration ≥ 12 months | 46%

16 HOW SUPPLIED/STORAGE AND HANDLING

ADSTILADRIN is shipped frozen at ≤ -60°C (≤ -76°F) in an insulated shipping box that will maintain the required temperature for a minimum of 72 hours after being sealed. Each carton (NDC 55566-1050-1) contains a removable cardboard nest of four (4) clear glass vials of ADSTILADRIN. Each vial contains a sterile frozen suspension with an extractable volume of 20 mL and is either sealed with a bromobutyl rubber stopper and a tamper-evident aluminum crimp (NDC 55566-1050-0) or with a bromobutyl rubber stopper embedded within a press-fit closure (NDC 55566-1050-2).

Upon receipt, cartons of ADSTILADRIN can be stored as indicated below:

- In a freezer ≤ -60°C (≤ -76°F) until expiry date printed on the carton.
- In a freezer between -25°C to -15°C (-13°F to 5°F) up to 3 months, without exceeding the original expiry date printed on the vial and outer carton.
  - When stored in freezer, the date of placement in freezer should be noted. In addition, the date for when the carton should be discarded if not used, must be written on the outer carton. These dates should be three months apart but should not past the original expiry date. This discard date supersedes the original expiry date.

When thawed, ADSTILADRIN is a clear to opalescent suspension, with nominal concentration of 3 × 10^11 viral particles (vp)/mL.

Prior to use, ADSTILADRIN must be brought to room temperature (20°C to 25°C [68°F to 77°F]). Once it is taken out of the freezer, the vials may be stored for up to 24 hours at room temperature and a total of up to 7 days refrigerated at 2°C to 8°C (36°F to 46°F), including thawing time.

After withdrawing the suspension into syringes, the syringes may be stored for up to 6 hours at room temperature (20°C to 25°C [68°F to 77°F]).

• Protect the vials from light. [see Dosage and Administration (2.2)].

• DO NOT REFREEZE

• ADSTILADRIN is a non-replicating adenoviral vector-based gene therapy. Follow universal biosafety precautions for handling [see Dosage and Administration (2.2)].

• Dispose of unused product and disposable materials that may have come in contact with ADSTILADRIN in accordance with local biosafety guidelines applicable for handling and disposal of the biohazard waste.

17 PATIENT COUNSELING INFORMATION

Risk of Metastatic Bladder Cancer with Delayed Cystectomy

- Inform patients that delaying cystectomy in patients with BCG-unresponsive CIS could lead to development of muscle-invasive or metastatic bladder cancer. Discuss the risk of muscle-invasive or metastatic bladder cancer and that the risk increases the longer cystectomy is delayed in the presence of persisting CIS [see Warnings and Precautions (5.1)].

Risk of Disseminated Adenovirus Infection

- Inform patients and their caregivers that treatment or contact with ADSTILADRIN in those who are immunocompromised, including those receiving immunosuppressive therapy, may increase the risk for disseminated adenovirus infection [see Warnings and Precautions (5.2)].

Shedding of ADSTILADRIN

Inform patients and their caregivers that transient and low‑level shedding of ADSTILADRIN may occur in urine. Instruct patients and their caregivers that for 2 days following treatment, voided urine should be disinfected for 15 minutes with an equal volume of bleach before flushing [see Dosage and Administration (2.2)].

Manufactured for:

Ferring Pharmaceuticals
2770 Kastrup, Denmark

U.S. License No. 2222

ADSTILADRIN®, Ferring and the Ferring Pharmaceuticals logo are trademarks of Ferring.

XXXXXXXXXX

PATIENT INFORMATION

ADSTILADRIN® (add-STILL-a-drin)

(nadofaragene firadenovec-vncg)

Suspension for Intravesical Use

Read this Patient Information before you have each ADSTILADRIN treatment. This information is not comprehensive and there may be new information.

How to get more information:

- Talk to your health care provider
- Call 1-888-337-7464

What is the most important information I should know about ADSTILADRIN?

- Individuals who are immunosuppressed or immune-deficient should not prepare, administer, receive or come into contact with ADSTILADRIN.

What is ADSTILADRIN used for?

- ADSTILADRIN is a prescription medicine for the treatment of a certain type of bladder cancer.

What is ADSTILADRIN?

- ADSTILADRIN is a therapy that contains a copy of the gene for human interferon alfa-2b.
- When administered into the bladder, the treatment delivers this gene, which is non-replicating, to cells in your bladder wall.
- Interferon alfa-2b has anti-tumor effects.
- The purpose of this gene therapy is to increase the level and length of time your bladder wall is exposed to interferon alfa-2b protein.

You should not receive ADSTILADRIN if:

- You have a sensitivity to interferon alfa or any of its components.

What should I tell my healthcare provider?

- Tell your doctor about all the medicines you take, including prescription and over-the-counter medicines, vitamins, and herbal supplements.

What are the possible side effects of ADSTILADRIN?

The most common side effects of ADSTILADRIN include:

- Urinary discharge
- Fatigue
- Bladder spasm
- Urgency to urinate
- Blood in your urine

These common side effects (above) are not all the possible side effects of ADSTILADRIN. For more information, ask your healthcare provider.

Call your doctor for medical advice about side effects. You may report side effects to FDA at 1-800-FDA-1088.

You may also report side effects to Ferring Pharmaceuticals at 1-888-337-7464.

How is ADSTILADRIN used?

- Once every 3 months your healthcare provider will administer 75 mL (about 2 and a half ounces) of ADSTILADRIN into your bladder through a urinary catheter and leave it there for 1 hour. During this time your healthcare provider may move you about every 15 minutes.

What other information should I know about using ADSTILADRIN?

Take these steps to prepare your toilet bowl after each treatment:

- Add about half a cup of bleach to the toilet bowl before you urinate.
- After urinating, wait 15 minutes before flushing the toilet.
- Repeat these steps every time you urinate for the first 2 days after treatment.

For more information, call 1-888-337-7464 or talk with your health care provider.

This Patient Information has been approved by the U.S. Food and Drug Administration.

Issued: Oct. 2025

Rx Only

Manufactured for:
Ferring Pharmaceuticals
2770 Kastrup, Denmark

ADSTILADRIN®, Ferring and the Ferring Pharmaceuticals logo are trademarks of Ferring.

PRINCIPAL DISPLAY PANEL - Outer Carton

NDC 55566-1050-1 Rx Only

nadofaragene firadenovec-vncg

ADSTILADRIN
75 mL Intravesical Suspension

Each carton contains 4 x 20 mL vials
Each vial contains 3 x 10^11 viral particles/mL

No U.S. standard of potency

For Intravesical Instillation Only

Sterile suspension
Preservative free
Discard unused portion

U.S. Licence No. 2222

Manufactured by:

Ferring Pharmaceuticals
2770 Kastrup, Denmark
Origin: Finland